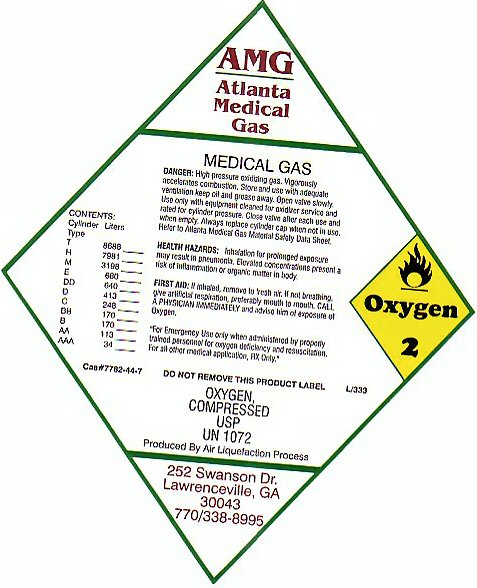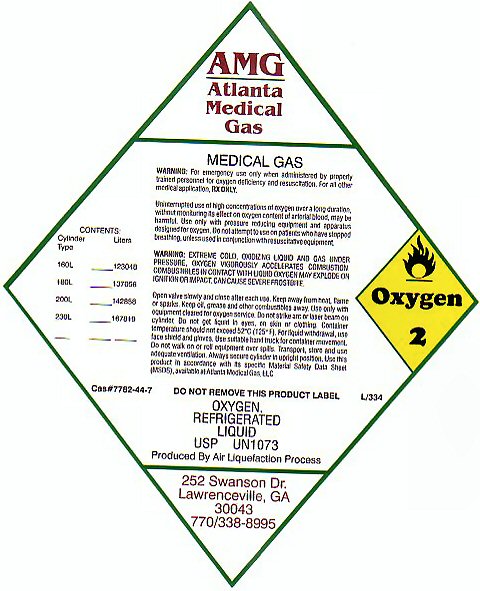 DRUG LABEL: Oxygen
NDC: 42165-0001 | Form: GAS
Manufacturer: Atlanta Medical Gas LLC
Category: prescription | Type: HUMAN PRESCRIPTION DRUG LABEL
Date: 20100101

ACTIVE INGREDIENTS: OXYGEN 99 L/100 L

OXYGEN COMPRESSED LABEL

MEDICAL GAS OXYGEN-2 OXYGEN COMPRESSED USP UN 1072 PRODUCED BY AIR LIQUEFACTION PROCESS

DANGER: HIGH PRESSURE OXIDIZING GAS. VIGOROUSLY ACCELERATES COMBUSTION. STORE AND USE WITH ADEQUATE VENTILATION KEEP OIL AND GREASE AWAY. OPEN VALVE SLOWLY. USE ONLY WITH EQUIPMENT CLEANED FOR OXYGEN SERVICE AND RATED FOR CYLINDER PRESSURE. CLOSE VALVE AFTER EACH USE AND WHEN EMPTY. ALWAYS REPLACE CYLINDER CAP WHEN NOT IN USE. REFER TO ATLANTA MEDICAL GAS MATERIAL SAFETY DATA SHEET.

HEALTH HAZARDS: INHALATION FOR PROLONGED EXPOSURE MAY RESULT IN PNEUMONIA. ELEVATED CONCENTRATIONS PRESENT A RISK OF INFLAMMATION OR ORGANIC MATTER IN BODY. FIRST AID: IF INHALED, REMOVE TO FRESH AIR. IF NOT BREATHING GIVE ARTIFICIAL RESPIRATION, PREFERABLY MOUTH TO MOUTH. CALL A PHYSICIAN IMMEDIATELY AND ADVISE HIM OF EXPOSURE TO OXYGEN.

FOR EMERGENCY USE ONLY WHEN ADMINISTERED BY PROPERLY TRAINED PERSONNEL FOR OXYGEN DEFICIENCY AND RESUSCITATION. FOR ALL OTHER MEDICAL APPLICATIONS Rx ONLY. CAS#7782-44-7 L/333

CONTENTS

CYLINDER TYPE LITERS

T 8688

H 7981

M 3198

E 680

DD 640

D 413

C 248

BB 170

B 170

AA 113

AAA 34

OXYGEN REFRIGERATED LIQUID

MEDICAL GAS OXYGEN-2 OXYGEN REFRIGERATED LIQUID USP UN1073 PRODUCED BY AIR LIQUEFACTION PROCESS

WARNING: FOR EMERGENCY USE ONLY WHEN ADMINISTERED BY PROPERLY TRAINED PERSONNEL FOR OXYGEN DEFICIENCY AND RESUSCITATION. FOR ALL OTHER MEDICAL APPLICATIONS Rx ONLY. UNINTERRUPTED USE OF HIGH CONCENTRATIONS OF OXYGEN OVER A LONG DURATION, WITHOUT MONITORING ITS EFFECT ON OXYGEN CONTENT OF ARTERIAL BLOOD MAY BE HARMFUL. USE ONLY WITH PRESSURE REDUCING EQUIPMENT AND APPARATUS DESIGNED FOR OXYGEN. DO NOT ATTEMPT TO USE ON PATIENTS WHO HAVE STOPPED BREATHING, UNLESS USED IN CONJUNCTION WITH RESUSCITATIVE EQUIPMENT.

WARNING: EXTREME COLD OXIDIZING LIQUID AND GAS UNDER PRESSURE. OXYGEN VIGOROUSLY ACCELERATES COMBUSTION. COMBUSTIBLES IN CONTACT WITH LIQUID OXYGEN MAY EXPLODE ON IGNITION OR IMPACT. CAN CAUSE SEVERE FROSTBITE. OPEN VALVE SLOWLY AND CLOSE AFTER EACH USE. KEEP AWAY FROM HEAT, FLAME, OR SPARKS. KEEP OIL, GREASE, AND OTHER COMBUSTIBLES AWAY. USE ONLY WITH EQUIPMENT CLEANED FOR OXYGEN SERVICE. DO NOT STRIKE ARC OR LASER BEAM ON CYLINDER. DO NOT GET LIQUID IN EYES, ON SKIN OR CLOTHING. CONTAINER TEMPERATURE SHOULD NOT EXCEED 52 C (125 F) FOR LIQUID WITHDRAWAL, USE FACE SHIELD AND GLOVES. USE SUITABLE HAND TRUCK FOR CONTAINER MOVEMENT. DO NOT WALK ON OR ROLL EQUIPMENT OVER SPILLS. TRANSPORT, STORE AND USE ADEQUATE VENTILATION. ALWAYS SECURE CYLINDER IN UPRIGHT POSITION. USE THIS PRODUCT IN ACCORDANCE WITH ITS SPECIFIC MATERIAL SAFETY DATA SHEET (MSDS), AVAILABLE AT ATLANTA MEDICAL GAS LLC. DO NOT REMOVE THIS PRODUCT LABEL. L/334 CAS# 7782-44-7

CONTENTS

CYLINDER TYPE LITERS

160L 123048

180L 137056

200L 142858

230L 167819